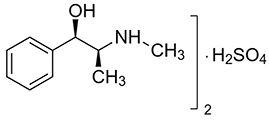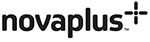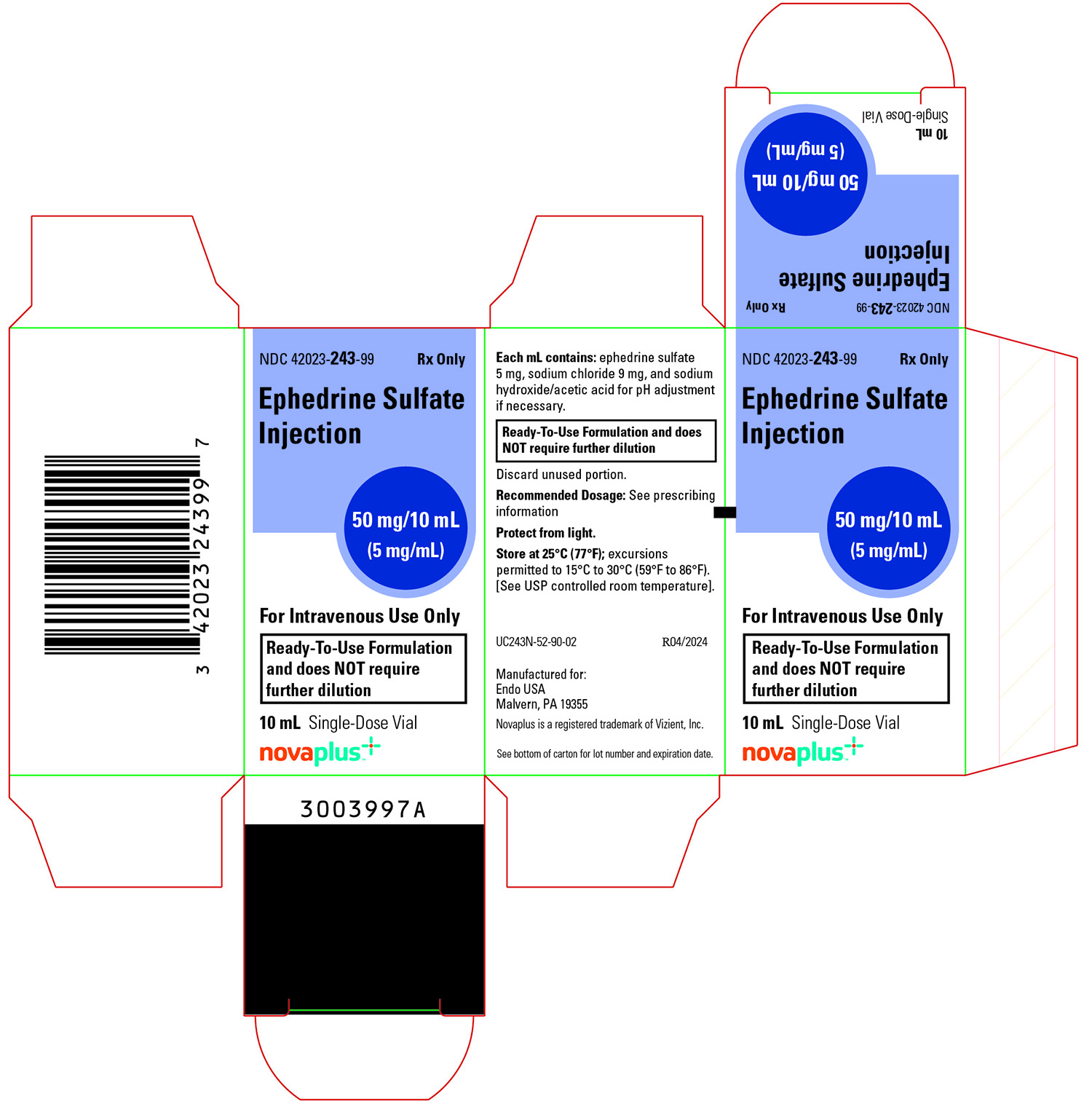 DRUG LABEL: EPHEDRINE SULFATE
NDC: 42023-243 | Form: INJECTION
Manufacturer: Endo USA, Inc.
Category: prescription | Type: HUMAN PRESCRIPTION DRUG LABEL
Date: 20240430

ACTIVE INGREDIENTS: EPHEDRINE SULFATE 5 mg/1 mL
INACTIVE INGREDIENTS: SODIUM CHLORIDE 9 mg/1 mL; ACETIC ACID; SODIUM HYDROXIDE

HIGHLIGHTS OF PRESCRIBING INFORMATION

These highlights do not include all the information needed to use EPHEDRINE SULFATE INJECTION safely and effectively. See full prescribing information for EPHEDRINE SULFATE INJECTION.
EPHEDRINE SULFATE INJECTION, for intravenous use
Initial U.S. Approval: 2016

1 INDICATIONS AND USAGE

Ephedrine Sulfate Injection is an alpha- and beta- adrenergic agonist and a norepinephrine-releasing agent that is indicated for the treatment of clinically important hypotension occurring in the setting of anesthesia. (1)

2 DOSAGE AND ADMINISTRATION

- Bolus intravenous injection: 5 mg to 10 mg (equivalent to 3.8 to 7.6 mg ephedrine base) as needed, not to exceed 50 mg. (2)
- Ready to Use formulation. Do not dilute.

3 DOSAGE FORMS AND STRENGTHS

Injection: 5 mg/mL ephedrine sulfate in a single-dose, 10 mL vial (50 mg/10 mL, equivalent to 38 mg ephedrine base) (3)

4 CONTRAINDICATIONS

None (4)

5 WARNINGS AND PRECAUTIONS

Pressor Effects with Concomitant Use with Oxytocic Drugs: Pressor effect of sympathomimetic pressor amines is potentiated (5.1)

Tachyphylaxis and Tolerance: Repeated administration of ephedrine may cause tachyphylaxis (5.2)

6 ADVERSE REACTIONS

Most common adverse reactions during treatment: nausea, vomiting, and tachycardia. (6)

To report SUSPECTED ADVERSE REACTIONS, contact Endo at 1-800-828-9393 or FDA at 1-800-FDA-1088 or www.fda.gov/medwatch.

7 DRUG INTERACTIONS

Interactions that Augment Pressor Effect: clonidine, oxytocin and oxytocic drugs, propofol, monoamine oxidase inhibitors (MAOIs), and atropine. Monitor blood pressure. (7)

Interactions that Antagonize the Pressor Effect: Antagonistic effects with α-adrenergic antagonists, β-adrenergic antagonists, reserpine, quinidine, mephentermine. Monitor blood pressure. (7)

Guanethidine: Ephedrine may inhibit the neuron blockage produced by guanethidine, resulting in loss of antihypertensive effectiveness. Monitor blood pressure and adjust the dosage of pressor accordingly.

Rocuronium: Ephedrine may reduce the onset time of neuromuscular blockade when used for intubation with rocuronium if administered simultaneously with anesthetic induction. Be aware of this potential interaction. No treatment or other interventions are needed.

Epidural anesthesia: Ephedrine may decrease the efficacy of epidural blockade by hastening the regression of sensory analgesia. Monitor and treat the patient according to clinical practice.

Theophylline: Concomitant use of ephedrine may increase the frequency of nausea, nervousness, and insomnia. Monitor patient for worsening symptoms and manage symptoms according to clinical practice.

Cardiac glycosides: Giving ephedrine with a cardiac glycoside, such as digitalis, may increase the possibility of arrhythmias. Carefully monitor patients on cardiac glycosides who are also administered ephedrine.

FULL PRESCRIBING INFORMATION

1 INDICATIONS AND USAGE

Ephedrine Sulfate Injection is indicated for the treatment of clinically important hypotension occurring in the setting of anesthesia.

2 DOSAGE AND ADMINISTRATION

2.1 General Dosage and Administration Instructions

Ready to Use formulation. Do not dilute.

Inspect parenteral drug products visually for particulate matter and discoloration prior to administration, whenever solution and container permit. Ephedrine Sulfate Injection is a clear, colorless solution. Do not use if discolored.

2.2 Dosing for the Treatment of Clinically Important Hypotension in the Setting of Anesthesia

The recommended dosages for the treatment of clinically important hypotension in the setting of anesthesia is an initial dose of 5 mg to 10 mg administered by intravenous bolus. Administer additional boluses as needed, not to exceed a total dosage of 50 mg.

• Adjust dosage according to the blood pressure goal (i.e., titrate to effect).

3 DOSAGE FORMS AND STRENGTHS

Ephedrine Sulfate Injection, 5 mg/mL is a clear, colorless solution available in a single-dose, 10 mL vial that contains 50 mg/10 mL ephedrine sulfate, equivalent to 38 mg ephedrine base.

4 CONTRAINDICATIONS

None

5 WARNINGS AND PRECAUTIONS

5.1 Pressor Effect with Concomitant Oxytocic Drugs

Serious postpartum hypertension has been described in patients who received both a vasopressor (i.e., methoxamine, phenylephrine, ephedrine) and an oxytocic (i.e., methylergonovine, ergonovine) [see Drug Interactions (7)]. Some of these patients experienced a stroke. Carefully monitor the blood pressure of individuals who have received both ephedrine and an oxytocic.

5.2 Tolerance and Tachyphylaxis

Data indicate that repeated administration of ephedrine can result in tachyphylaxis. Clinicians treating anesthesia-induced hypotension with Ephedrine Sulfate Injection should be aware of the possibility of tachyphylaxis and should be prepared with an alternative pressor to mitigate unacceptable responsiveness.

5.3 Risk of Hypertension When Used Prophylactically

When used to prevent hypotension, ephedrine has been associated with an increased incidence of hypertension compared with when ephedrine is used to treat hypotension.

6 ADVERSE REACTIONS

The following adverse reactions associated with the use of ephedrine sulfate were identified in the literature. Because these reactions are reported voluntarily from a population of uncertain size, it is not always possible to estimate their frequency reliably or to establish a causal relationship to drug exposure.

Gastrointestinal disorders: Nausea, vomiting

Cardiac disorders: Tachycardia, palpitations (thumping heart), reactive hypertension, bradycardia, ventricular ectopics, R-R variability

Nervous system disorders: Dizziness

Psychiatric disorders: Restlessness

7 DRUG INTERACTIONS

Interactions that Augment the Pressor Effect
Oxytocin and oxytocic drugs
Clinical Impact: | Serious postpartum hypertension has been described in patients who received both a vasopressor (i.e., methoxamine, phenylephrine, ephedrine) and an oxytocic (i.e., methylergonovine, ergonovine). Some of these patients experienced a stroke.
Intervention: | Carefully monitor the blood pressure of individuals who have received both ephedrine and an oxytocic.
Clonidine, propofol, monoamine oxidase inhibitors (MAOIs), atropine
Clinical Impact: | These drugs augment the pressor effect of ephedrine.
Intervention: | Carefully monitor the blood pressure of individuals who have received both ephedrine and any of these drugs.
Interactions that Antagonize the Pressor Effect
Clinical Impact: | These drugs antagonize the pressor effect of ephedrine.
Intervention: | Carefully monitor the blood pressure of individuals who have received both ephedrine and any of these drugs.
Examples: | α-adrenergic antagonists, β-adrenergic receptor antagonists, reserpine, quinidine, mephentermine
Other Drug Interactions
Guanethidine
Clinical Impact: | Ephedrine may inhibit the neuron blockage produced by guanethidine, resulting in loss of antihypertensive effectiveness.
Intervention: | Clinician should monitor patient for blood pressor response and adjust the dosage or choice of pressor accordingly.
Rocuronium
Clinical Impact: | Ephedrine may reduce the onset time of neuromuscular blockade when used for intubation with rocuronium if administered simultaneously with anesthetic induction.
Intervention: | Be aware of this potential interaction. No treatment or other interventions are needed.
Epidural anesthesia
Clinical Impact: | Ephedrine may decrease the efficacy of epidural blockade by hastening the regression of sensory analgesia.
Intervention: | Monitor and treat the patient according to clinical practice.
Theophylline
Clinical Impact: | Concomitant use of ephedrine may increase the frequency of nausea, nervousness, and insomnia.
Intervention: | Monitor patient for worsening symptoms and manage symptoms according to clinical practice.
Cardiac glycosides
Clinical Impact: | Giving ephedrine with a cardiac glycoside, such as digitalis, may increase the possibility of arrhythmias.
Intervention: | Carefully monitor patients on cardiac glycosides who are also administered ephedrine.

8 USE IN SPECIFIC POPULATIONS

8.1 Pregnancy

Risk Summary

Available data from randomized studies, case series, and reports of ephedrine sulfate use in pregnant women have not identified a drug-associated risk of major birth defects, miscarriage, or adverse maternal or fetal outcomes. However, there are clinical considerations (see Clinical Considerations). In animal reproduction studies, decreased fetal survival and fetal body weights were observed in the presence of maternal toxicity after normotensive pregnant rats were administered 60 mg/kg intravenous ephedrine sulfate (12 times the maximum recommended human dose (MRHD) of 50 mg/day). No malformations or embryofetal adverse effects were observed when pregnant rats or rabbits were treated with intravenous bolus doses of ephedrine sulfate during organogenesis at doses 1.9 and 7.7 times the MRHD, respectively (see Data).

The estimated background risk of major birth defects and miscarriage for the indicated population are unknown. All pregnancies have a background risk of birth defect, loss, or other adverse outcomes. In the U.S. general population, the estimated background risk of major birth defects and miscarriage in clinically recognized pregnancies is 2 to 4% and 15 to 20%, respectively.

Clinical Considerations

Disease-associated maternal and/or embryofetal risk

Untreated hypotension associated with spinal anesthesia for cesarean section is associated with an increase in maternal nausea and vomiting. A decrease in uterine blood flow due to maternal hypotension may result in fetal bradycardia and acidosis.

Fetal/Neonatal Adverse Reactions

Cases of potential metabolic acidosis in newborns at delivery with maternal ephedrine exposure have been reported in the literature. These reports describe umbilical artery pH of ≤7.2 at the time of delivery [see Clinical Pharmacology (12.3)]. Monitoring of the newborn for signs and symptoms of metabolic acidosis may be required. Monitoring of infant’s acid‐base status is warranted to ensure that an episode of acidosis is acute and reversible.

Data

Animal Data

Decreased fetal body weights were observed when pregnant rats were administered intravenous bolus doses of 60 mg/kg ephedrine sulfate (12 times the maximum recommended human dose (MRHD) of 50 mg based on body surface area) from Gestation Day 6-17. This dose was associated with evidence of maternal toxicity (decreased body weight of dams and abnormal head movements). No malformations or fetal deaths were noted at this dose. No effects on fetal body weight were noted at 10 mg/kg (1.9 times the MRHD of 50 mg).

No evidence of malformations or embryo-fetal toxicity were noted in pregnant rabbits administered intravenous bolus doses up to 20 mg/kg ephedrine sulfate (7.7 times the maximum recommended human dose (MRHD) of 50 mg based on body surface area) from Gestation Day 6-20. This dose was associated with expected pharmacological maternal effects (increased respiration rate, dilated pupils, piloerection).

Decreased fetal survival and body weights in the presence of maternal toxicity (increased mortality) were noted when pregnant dams were administered intravenous bolus doses of 60 mg/kg epinephrine sulfate (approximately 12 times the MRHD based on body surface area) from GD 6 through Lactation Day 20. No adverse effects were noted at 10 mg/kg (1.9 times the MRHD).

8.2 Lactation

Risk Summary

A single published case report indicates that ephedrine is present in human milk. However, no information is available on the effects of the drug on the breastfed infant or the effects of the drug on milk production. The developmental and health benefits of breastfeeding should be considered along with the mother's clinical need for Ephedrine Sulfate Injection and any potential adverse effects on the breastfed child from Ephedrine Sulfate Injection or from the underlying maternal condition.

8.4 Pediatric Use

Safety and effectiveness in pediatric patients have not been established.

Animal Toxicity Data

In a study in which juvenile rats were administered intravenous bolus doses of 2, 10, or 60 mg/kg ephedrine sulfate daily from Postnatal Day 35 to 56, an increased incidence of mortality was noted at the high dose of 60 mg/kg. The no-adverse-effect level was 10 mg/kg (approximately 1.9 times a maximum daily dose of 50 mg in a 60 kg person based on body surface area).

8.5 Geriatric Use

Clinical studies of ephedrine did not include sufficient numbers of subjects aged 65 and over to determine whether they respond differently from younger subjects. Other reported clinical experience has not identified differences in responses between the elderly and younger patients. In general, dose selection for an elderly patient should be cautious, usually starting at the low end of the dosing range, reflecting the greater frequency of decreased hepatic, renal, or cardiac function, and of concomitant disease or other drug therapy.

This drug is known to be substantially excreted by the kidney, and the risk of adverse reactions to this drug may be greater in patients with impaired renal function. Because elderly patients are more likely to have decreased renal function, care should be taken in dose selection, and it may be useful to monitor renal function.

8.6 Renal Impairment

Ephedrine and its metabolite are excreted in urine. In patients with renal impairment, excretion of ephedrine is likely to be affected with a corresponding increase in elimination half-life, which will lead to slow elimination of ephedrine and consequently prolonged pharmacological effect and potentially adverse reactions. Monitor patients with renal impairment carefully after the initial bolus dose for adverse events.

10 OVERDOSAGE

Overdose of ephedrine can cause a rapid rise in blood pressure. In the case of an overdose, careful monitoring of blood pressure is recommended. If blood pressure continues to rise to an unacceptable level, parenteral antihypertensive agents can be administered at the discretion of the clinician.

11 DESCRIPTION

Ephedrine is an alpha- and beta-adrenergic agonist and a norepinephrine-releasing agent. Ephedrine Sulfate Injection, 5 mg/mL is a clear, colorless, sterile, ready-to-use solution for intravenous injection. The chemical name of ephedrine sulfate is (1R,2S)-(-)-2-methylamine-1-phenylpropan-1-ol sulfate, and the molecular weight is 428.5 g/mol. Its molecular formula is (C10H15NO)2 · H2SO4 and its structural formula is depicted below:

Ephedrine sulfate is freely soluble in water and ethanol, very slightly soluble in chloroform, and practically insoluble in ether. Each mL contains ephedrine sulfate 5 mg (equivalent to 3.8 mg ephedrine base), sodium chloride 9 mg, and sodium hydroxide and/or acetic acid for pH adjustment, if necessary. The pH range is 4.5 to 7.0.

12 CLINICAL PHARMACOLOGY

12.1 Mechanism of Action

Ephedrine sulfate is a sympathomimetic amine that directly acts as an agonist at α- and β-adrenergic receptors and indirectly causes the release of norepinephrine from sympathetic neurons. Pressor effects by direct alpha- and beta-adrenergic receptor activation are mediated by increases in arterial pressures, cardiac output, and peripheral resistance. Indirect adrenergic stimulation is caused by norepinephrine release from sympathetic nerves.

12.2 Pharmacodynamics

Ephedrine stimulates heart rate and cardiac output and variably increases peripheral resistance; as a result, ephedrine usually increases blood pressure. Stimulation of the α-adrenergic receptors of smooth muscle cells in the bladder base may increase the resistance to the outflow of urine. Activation of β-adrenergic receptors in the lungs promotes bronchodilation.

The overall cardiovascular effect from ephedrine is the result of a balance among α-1 adrenoceptor-mediated vasoconstriction, β-2 adrenoceptor-mediated vasoconstriction, and β-2 adrenoceptor-mediated vasodilatation. Stimulation of the β-1 adrenoceptors results in positive inotrope and chronotrope action.

Tachyphylaxis to the pressor effects of ephedrine may occur with repeated administration [see Warnings and Precautions 5.2].

12.3 Pharmacokinetics

Publications studying pharmacokinetics of oral administration of (-)-ephedrine support that (‑)‑ephedrine is metabolized into norephedrine. However, the metabolism pathway is unknown. Both the parent drug and the metabolite are excreted in urine. Limited data after IV administration of ephedrine support similar observations of urinary excretion of drug and metabolite. The plasma elimination half-life of ephedrine following oral administration was about 6 hours.

Ephedrine crosses the placental barrier [see Use in Specific Populations 8.1].

13 NONCLINICAL TOXICOLOGY

13.1 Carcinogenesis, Mutagenesis, Impairment of Fertility

Carcinogenesis: Two-year feeding studies in rats and mice conducted under the National Toxicology Program (NTP) demonstrated no evidence of carcinogenic potential with ephedrine sulfate at doses up to 10 mg/kg/day and 27 mg/kg/day (approximately 2 times and 3 times the maximum human recommended dose on a mg/m^2 basis, respectively).

Mutagenesis: Ephedrine sulfate tested negative in the in vitro bacterial reverse mutation assay, the in vitro mouse lymphoma assay, the in vitro sister chromatid exchange, the in vitro chromosomal aberration assay, and the in vivo rat bone marrow micronucleus assay.

Impairment of Fertility: There was no impact on fertility or early embryonic development in a study in which male rats were administered intravenous bolus doses of 0, 2, 10, or 60 mg/kg ephedrine sulfate (up to 12 times the maximum recommended human dose of 50 mg based on body surface area) for 28 days prior to mating and through gestation and females were treated for 14 days prior to mating through Gestation Day 7.

14 CLINICAL STUDIES

The evidence for the efficacy of ephedrine injection is derived from the published literature. Increases in blood pressure following administration of ephedrine were observed in 14 studies, including 9 where ephedrine was used in pregnant women undergoing neuraxial anesthesia during Cesarean delivery, 1 study in non-obstetric surgery under neuraxial anesthesia, and 4 studies in patients undergoing surgery under general anesthesia. Ephedrine has been shown to raise systolic and mean blood pressure when administered as a bolus dose following the development of hypotension during anesthesia.

16 HOW SUPPLIED/STORAGE AND HANDLING

Ephedrine Sulfate Injection 50 mg/10 mL (5 mg/mL, equivalent to 3.8 mg/mL ephedrine base), is a clear, colorless solution and is supplied as follows:

NDC | Strength | How Supplied
42023-243-99 | 50 mg/10 mL (5 mg/mL) | 10 mL clear, glass, single-dose vial; (supplied in packages of 1)

Vial stoppers are not manufactured with natural rubber latex. Store Ephedrine Sulfate Injection, 5 mg/mL at 25°C (77°F); excursions permitted to 15°C to 30°C (59°F to 86°F) [see USP Controlled Room Temperature]. Store in carton until time of use. For single use only. Discard unused portion.

Manufactured for:

Endo USA

Malvern, PA 19355

© 2024 Endo, Inc. or one of its affiliates.

Novaplus is a registered trademark of Vizient, Inc.

04/2024

PRINCIPAL DISPLAY PANEL - 1 X 10 mL Single-Dose Vial Carton

Ephedrine Sulfate Injection 10 mL Single-Dose Vial carton